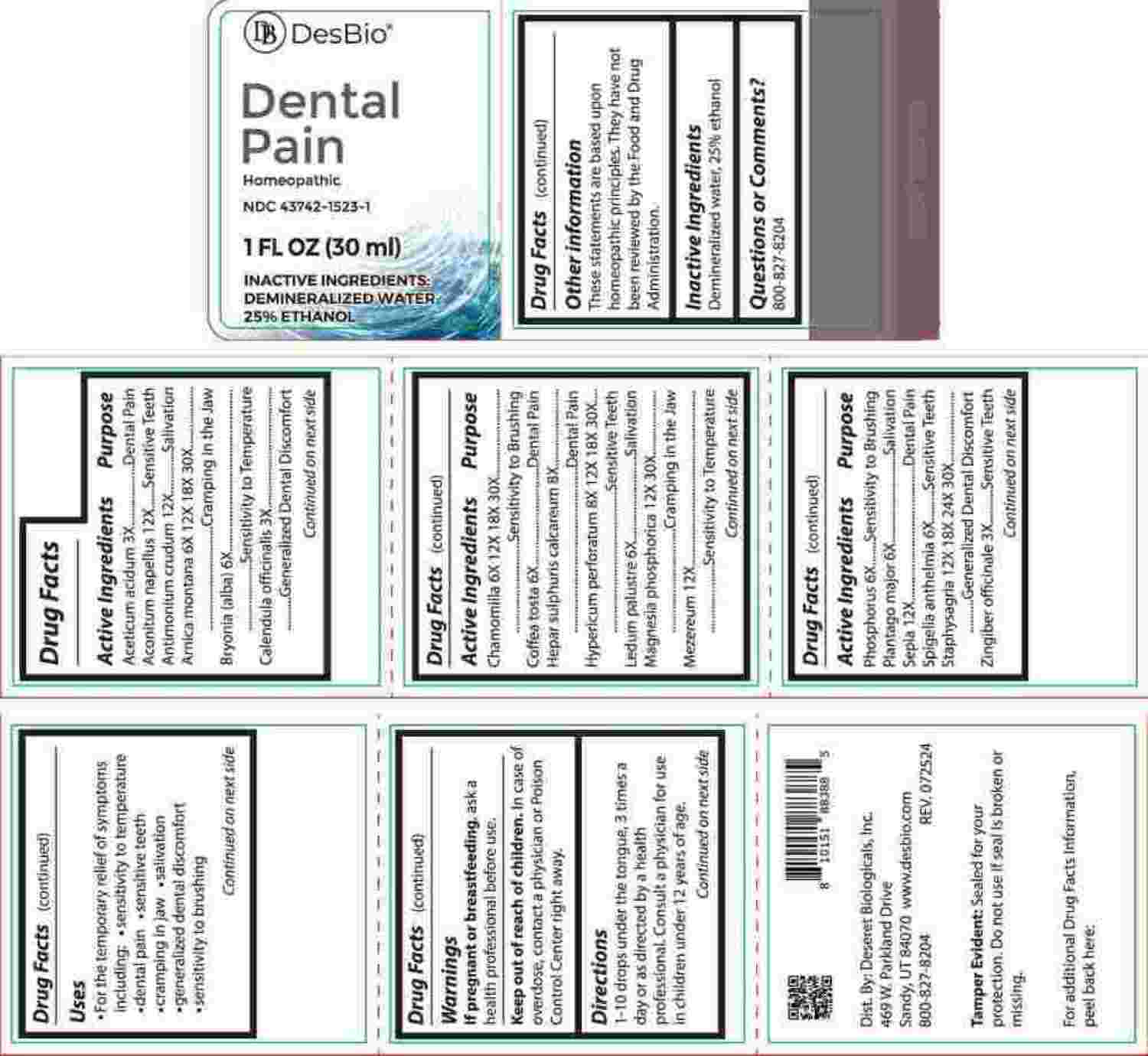 DRUG LABEL: Dental Pain
NDC: 43742-1523 | Form: LIQUID
Manufacturer: Deseret Biologicals, Inc.
Category: homeopathic | Type: HUMAN OTC DRUG LABEL
Date: 20241023

ACTIVE INGREDIENTS: ACETIC ACID 3 [hp_X]/1 mL; CALENDULA OFFICINALIS FLOWERING TOP 3 [hp_X]/1 mL; GINGER 3 [hp_X]/1 mL; BRYONIA ALBA ROOT 6 [hp_X]/1 mL; COFFEA ARABICA SEED, ROASTED 6 [hp_X]/1 mL; RHODODENDRON TOMENTOSUM LEAFY TWIG 6 [hp_X]/1 mL; PHOSPHORUS 6 [hp_X]/1 mL; PLANTAGO MAJOR WHOLE 6 [hp_X]/1 mL; SPIGELIA ANTHELMIA WHOLE 6 [hp_X]/1 mL; ARNICA MONTANA WHOLE 6 [hp_X]/1 mL; MATRICARIA CHAMOMILLA WHOLE 6 [hp_X]/1 mL; CALCIUM SULFIDE 8 [hp_X]/1 mL; HYPERICUM PERFORATUM WHOLE 8 [hp_X]/1 mL; ACONITUM NAPELLUS WHOLE 12 [hp_X]/1 mL; ANTIMONY TRISULFIDE 12 [hp_X]/1 mL; DAPHNE MEZEREUM BARK 12 [hp_X]/1 mL; SEPIA OFFICINALIS JUICE 12 [hp_X]/1 mL; DELPHINIUM STAPHISAGRIA SEED 12 [hp_X]/1 mL; MAGNESIUM PHOSPHATE, DIBASIC TRIHYDRATE 12 [hp_X]/1 mL
INACTIVE INGREDIENTS: WATER; ALCOHOL

DRUG FACTS:

ACTIVE INGREDIENTS:

Aceticum Acidum 3X, Aconitum Napellus 12X, Antimonium Crudum 12X, Arnica Montana 6X, 12X, 18X, 30X, Bryonia (Alba) 6X, Calendula Officinalis 3X, Chamomilla 6X, 12X, 18X, 30X, Coffea Tosta 6X, Hepar Sulphuris Calcareum 8X, Hypericum Perforatum 8X, 12X, 18X, 30X, Ledum Palustre 6X, Magnesia Phosphorica 12X, 30X, Mezereum 12X, Phosphorus 6X, Plantago Major 6X, Sepia 12X, Spigelia Anthelmia 6X, Staphysagria 12X, 18X, 24X, 30X, Zingiber Officinale 3X.

PURPOSE:

Aceticum Acidum – Dental Pain, Aconitum Napellus – Sensitive Teeth, Antimonium Crudum - Salivation, Arnica Montana – Cramping in the Jaw, Bryonia (Alba) – Sensitivity to Temperature, Calendula Officinalis – Sensitivity to Brushing, Chamomilla – Sensitivity to Brushing, Coffea Tosta – Dental Pain, Hepar Sulphuris Calcareum – Dental Pain, Hypericum Perforatum – Sensitive Teeth, Ledum Palustre - Salivation, Magnesia Phosphorica – Cramping in the Jaw, Mezereum – Sensitivity to Temperature, Phosphorus – Sensitivity to Brushing, Plantago Major - Salivation, Sepia – Dental Pain, Spigelia Anthelmia – Sensitive Teeth, Staphysagria – Generalized Dental Discomfort, Zingiber Officinale – Sensitive Teeth

USES:

• For the temporary relief of symptoms including:

• sensitivity to temperature • dental pain • sensitive teeth • cramping in jaw

• salivation • generalized dental discomfort • sensitivity to brushing

These statements are based upon homeopathic principles. They have not been reviewed by the Food and Drug Administration.

WARNINGS:

If pregnant or breast-feeding, ask a health professional before use.

Keep out of reach of children. In case of overdose, Contact a physician or Poison Control Center right away.

Tamper Evident: Sealed for your protection. Do not use if seal is broken or missing.

KEEP OUT OF REACH OF CHILDREN:

In case of overdose, contact a physician or Poison Control Center right away.

DIRECTIONS:

1-10 drops under the tongue, 3 times a day or as directed by a health professional. Consult a physician for use in children under 12 years of age.

INACTIVE INGREDIENTS:

Demineralized water, 25% ethanol

QUESTIONS:

Dist. By: Deseret Biologicals, Inc.

469 W. Parkland Drive

Sandy, UT 84070

www.desbio.com

800-827-8204

PACKAGE LABEL DISPLAY:

DesBio

Dental Pain

Homeopathic
NDC 43742-1523-1
1 FL OZ (30 ml)